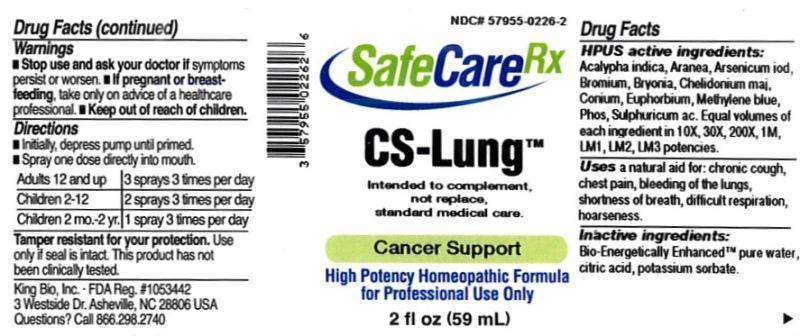 DRUG LABEL: CS Lung
NDC: 57955-0226 | Form: LIQUID
Manufacturer: King Bio Inc.
Category: homeopathic | Type: HUMAN OTC DRUG LABEL
Date: 20150625

ACTIVE INGREDIENTS: ACALYPHA INDICA 10 [hp_X]/59 mL; ARANEUS DIADEMATUS 10 [hp_X]/59 mL; ARSENIC TRIIODIDE 10 [hp_X]/59 mL; BROMINE 10 [hp_X]/59 mL; BRYONIA ALBA ROOT 10 [hp_X]/59 mL; CHELIDONIUM MAJUS 10 [hp_X]/59 mL; CONIUM MACULATUM FLOWERING TOP 10 [hp_X]/59 mL; EUPHORBIA RESINIFERA RESIN 10 [hp_X]/59 mL; METHYLENE BLUE 10 [hp_X]/59 mL; PHOSPHORUS 10 [hp_X]/59 mL; SULFURIC ACID 10 [hp_X]/59 mL
INACTIVE INGREDIENTS: WATER; ANHYDROUS CITRIC ACID; POTASSIUM SORBATE

CS Lung™

ACTIVE INGREDIENT

Drug Facts__________________________________________________________________________________________________________

HPUS active ingredients: Acalypha indica, Aranea diadema, Arsenicum iodatum, Bromium, Bryonia, Chelidonium majus, Conium maculatum, Euphorbium officinarum, Methylene blue, Phosphorus, Sulphuricum acidum. Equal volumes of each ingredient in 10X, 30X, 200X, 1M, LM1, LM2, LM3 potencies.

INDICATIONS AND USAGE

Uses a natural aid for: chronic cough, chest pain, bleeding of the lungs, shortness of breath, difficult respiration, hoarseness.

Inactive Ingredients:

Bio-Energetically Enhanced™ pure water, citric acid and potassium sorbate.

Warnings

- Stop use and ask your doctor if symptoms persist or worsen.
- If pregnant or breast-feeding, take only on advice of a healthcare professional.

- Keep out of reach of children.

Directions

- Initially, depress pump until primed.
- Spray one dose directly into mouth.
- Adults 12 and up: 3 sprays 3 times per day.
- Children 2-12: 2 sprays 3 times per day.
- Children 2 mo.-2yr: 1 spray 3 times per day.

OTHER SAFETY INFORMATION

Tamper resistant for your protection. Use only if safety seal is intact. This product has not been clinically tested. Intended to complement, not replace, standard medical care.

PURPOSE

Uses a natural aid for:

- chronic cough
- chest pain
- bleeding of the lungs
- shortness of breath
- difficult respiration
- hoarseness